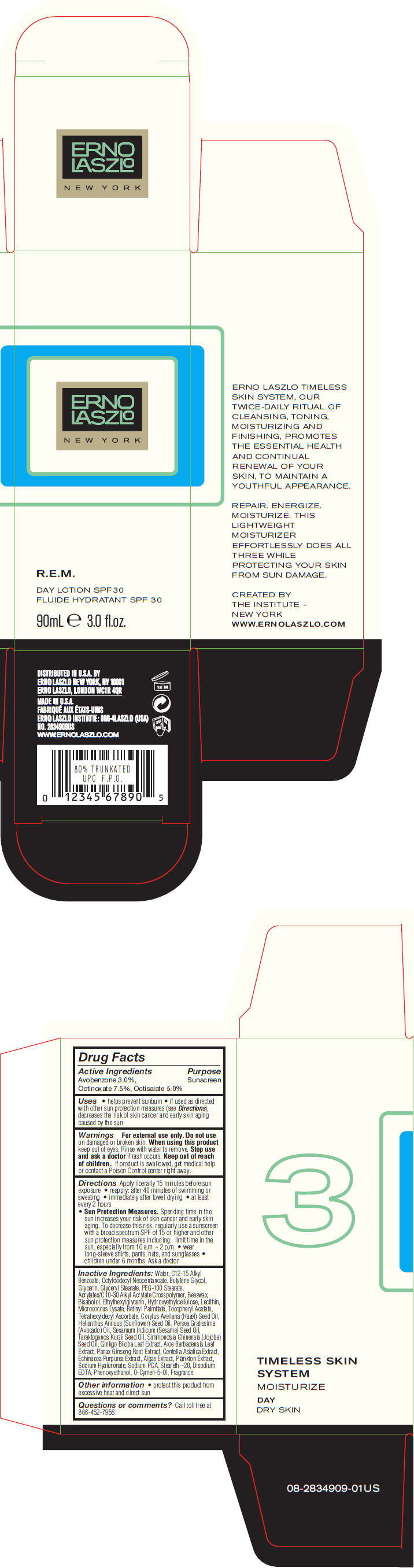 DRUG LABEL: R.E.M. Day  SPF 30
NDC: 57913-2834 | Form: LOTION
Manufacturer: Erno Laszlo, Inc.
Category: otc | Type: HUMAN OTC DRUG LABEL
Date: 20130410

ACTIVE INGREDIENTS: Avobenzone 30 mg/1 mL; Octinoxate 75 mg/1 mL; Octisalate 50 mg/1 mL
INACTIVE INGREDIENTS: Water; Alkyl (C12-15) Benzoate; Octyldodecyl Neopentanoate; Butylene Glycol; Glycerin; Glyceryl Monostearate; PEG-100 Stearate; Yellow Wax; Levomenol; Ethylhexylglycerin; Vitamin A Palmitate; .Alpha.-Tocopherol Acetate; Tetrahexyldecyl Ascorbate; European Hazelnut Oil; Sunflower Oil; Avocado Oil; Sesame Oil; Hydnocarpus Kurzii Seed Oil; Jojoba Oil; Ginkgo; Aloe Vera Leaf; Asian Ginseng; Centella Asiatica; Echinacea Purpurea; Hyaluronate Sodium; Sodium Pyrrolidone Carboxylate; Steareth-20; Edetate Disodium; Phenoxyethanol; O-Cymen-5-Ol

R.E.M. Day SPF 30

Drug Facts

Active Ingredients

Avobenzone 3.0%, Octinoxate 7.5%, Octisalate 5.0%

Purpose

Sunscreen

Uses

- helps prevent sunburn
- if used as directed with other sun protection measures (see Directions), decreases the risk of skin cancer and early skin aging caused by the sun

Warnings

For external use only.

Do not use on damaged or broken skin.

When using this product keep out of eyes. Rinse with water to remove.

Stop use and ask a doctor if rash occurs.

Keep out of reach of children. If product is swallowed, get medical help or contact a Poison Control center right away.

Directions

Apply liberally 15 minutes before sun exposure

- reapply: after 40 minutes of swimming or sweating
- immediately after towel drying
- at least every 2 hours
- Sun Protection Measures. Spending time in the sun increases your risk of skin cancer and early skin aging. To decrease this risk, regularly use a sunscreen with a broad spectrum SPF of 15 or higher and other sun protection measures including: limit time in the sun, especially from 10 a.m. - 2 p.m.
  - wear long-sleeve shirts, pants, hats, and sunglasses
  - children under 6 months: Ask a doctor

Inactive Ingredients

Water, C12-15 Alkyl Benzoate, Octyldodecyl Neopentanoate, Butylene Glycol, Glycerin, Glyceryl Stearate, PEG-100 Stearate, Acrylates/C10-30 Alkyl Acrylate Crosspolymer, Beeswax, Bisabolol, Ethylhexylglycerin, Hydroxyethylcellulose, Lecithin, Micrococcus Lysate, Retinyl Palmitate, Tocopheryl Acetate, Tetrahexyldecyl Ascorbate, Corylus Avellana (Hazel) Seed Oil, Helianthus Annuus (Sunflower) Seed Oil, Persea Gratissima (Avocado) Oil, Sesamum Indicum (Sesame) Seed Oil, Taraktogenos Kurzii Seed Oil, Simmondsia Chinensis (Jojoba) Seed Oil, Ginkgo Biloba Leaf Extract, Aloe Barbadensis Leaf Extract, Panax Ginseng Root Extract, Centella Asiatica Extract, Echinacea Purpurea Extract, Algae Extract, Plankton Extract, Sodium Hyaluronate, Sodium PCA, Steareth –20, Disodium EDTA, Phenoxyethanol, O-Cymen-5-Ol, Fragrance.

Other information

- protect this product from excessive heat and direct sun

Questions or comments?

Call toll free at 866-452-7956.

DISTRIBUTED IN U.S.A. BY
ERNO LASZLO NEW YORK, NY 10001

PRINCIPAL DISPLAY PANEL - 90 mL Bottle Carton

ERNO
LASZLO

NEW YORK

R.E.M.

DAY LOTION SPF 30

90mL e 3.0 fl.oz.